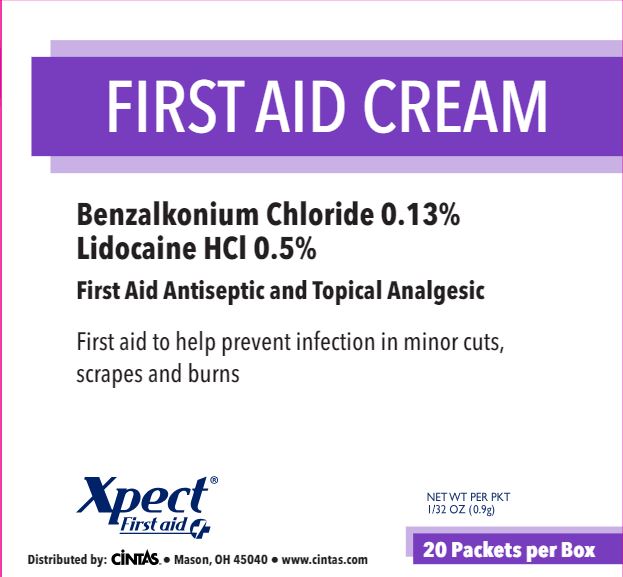 DRUG LABEL: Xpect First Aid Cream
NDC: 42961-259 | Form: CREAM
Manufacturer: Cintas Corporation
Category: otc | Type: HUMAN OTC DRUG LABEL
Date: 20250930

ACTIVE INGREDIENTS: BENZALKONIUM CHLORIDE .13 g/100 g; LIDOCAINE HCL .5 g/100 g
INACTIVE INGREDIENTS: ALOE VERA LEAF; ALCOHOL; METHYLPARABEN; MINERAL OIL; PARAFFIN; PROPYLPARABEN; WATER; PETROLATUM; WHITE WAX

Xpect First Aid Cream

Active ingredients

Benzalkonium chloride 0.13%

Lidocaine HCl 0.5%

Purpose

First aid antiseptic

Topical analgesic

Uses

- temporary relief of pain associated with minor cuts, scrapes, and burns
- helps protect against harmful bacteria

Warnings

For external use only.

Do not use

- in eyes
- in large quantities
- over raw, or blistered areas, or on deep puncture wounds, animal bites, or serious burns
- for more than one week unless directed by a doctor.

Stop use and ask a doctor if

- the condition worsens or if symptoms persist for more than 7 days or clear up and occur again within a few days.

Keep out of reach of children. If swallowed, get medical help or contact a Poison Control Center right away.

Directions

- adults and children 2 years and over: clean affected area, apply small amount no more than 3 times daily, may be covered with a sterile bandage
- children under 2 years: do not use, consult a doctor

Other information

- store at room temperature (do not freeze)
- do not use any opened or torn packets

Inactive ingredients

aloe vera, cetearyl alcohol*, disodium EDTA*, emulsifying wax*, ethyl alcohol*, ethylhexylglcerin*, glycerin*, glyceryl stearate/PEG100 stearate*, maltodextrin*, methylparaben*, mineral oil, paraffin*, phenoxyethanol*, propylene glycol*, propylparaben*, purified water, stearic acid*, sodium hydroxide*, white petrolatum*, white wax*
* may contain ingredient

Questions or comments?

Call 1-877-973-2811

Monday-Friday 8 AM-5PM EST

Principal Display Panel

FIRST AID CREAM

Active Ingredients:

Benzalkonium Chloride 0.13%

Lidocaine HCl 0.5%

First Aid Antiseptic and Topical Analgesic

First aid to help prevent infection in minor cuts, scrapes, and burns.

Xpect® First aid

Distributed by: Cintas® • Mason, OH 45040 • www.cintas.com

NET WT. PER PACKET 1/32 OZ (0.9g)

20 Packets per Box